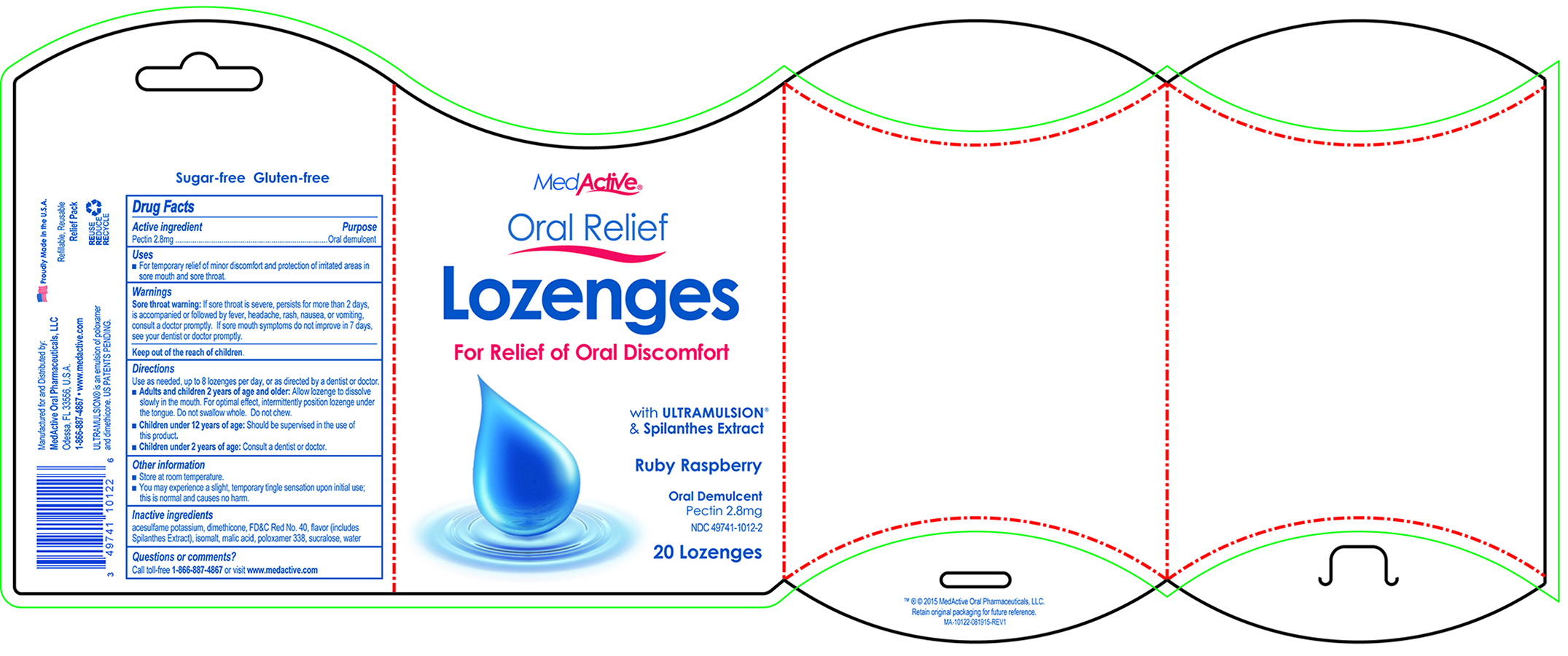 DRUG LABEL: MedActive Oral Relief
NDC: 49741-1012 | Form: LOZENGE
Manufacturer: Integrate Oral Care, LLC.
Category: otc | Type: HUMAN OTC DRUG LABEL
Date: 20221230

ACTIVE INGREDIENTS: PECTIN 2.8 mg/1 1
INACTIVE INGREDIENTS: FD&C RED NO. 40; DIMETHICONE; MALIC ACID; SUCRALOSE; ISOMALT; POLOXAMER 338; WATER; ACESULFAME POTASSIUM

Active Ingredient (in each lozenge)

Pectin 2.8 mg

Purpose

Oral Demulcent

Uses

- For temporary relief of minor discomfort and protection of irritated areas in sore mouth and sore throat.

WARNINGS

Sore Throat warning: If sore throat is severe, persists for more than 2 days, is accompanied or followed by fever, headache, rash, nausea, or vomiting, consult a doctor promptly. If sore mouth symptons do not improve in 7 days, see your dentist or doctor promptly.

Keep out of the reach of children.

Directions

Use as needed, up to 8 lozenges per day, or as directed by a dentist or doctor.

- Adults and children 2 years of age and older: Allow lozenge to dissolve slowly in the mouth. For optimal effect, intermittently position lozenge under the tongue. Do not swallow whole. Do not chew.
- Children under 12 years or age: Should be supervised in the use of this product.
- Children under 2 years of age: Consult a dentist or doctor.

Other Information

- Store at room temperature.
- You may experience a slight, temporary tingle sensation upon initial use; this is normal and causes no harm.

Inactive Ingredients

acesulfame potassium, dimethicone, FD&C Red No. 40, flavor (includes Spilanthes Extract), isomalt, malic acid, poloxamer 338, sucralose, water

Questions or comments?

Call toll-free 1-866-887-4867 or visit www.integrateoralcare.com

PACKAGE LABEL

MedActive® Oral Relief Lozenges

For Relief of Oral Discomfort

with ULTRAMULSION® & Spilanthes Extract

Ruby Raspberry

Oral Demulcent

Pectin 2.8mg

NDC 49741-1012-2

20 Lozenges